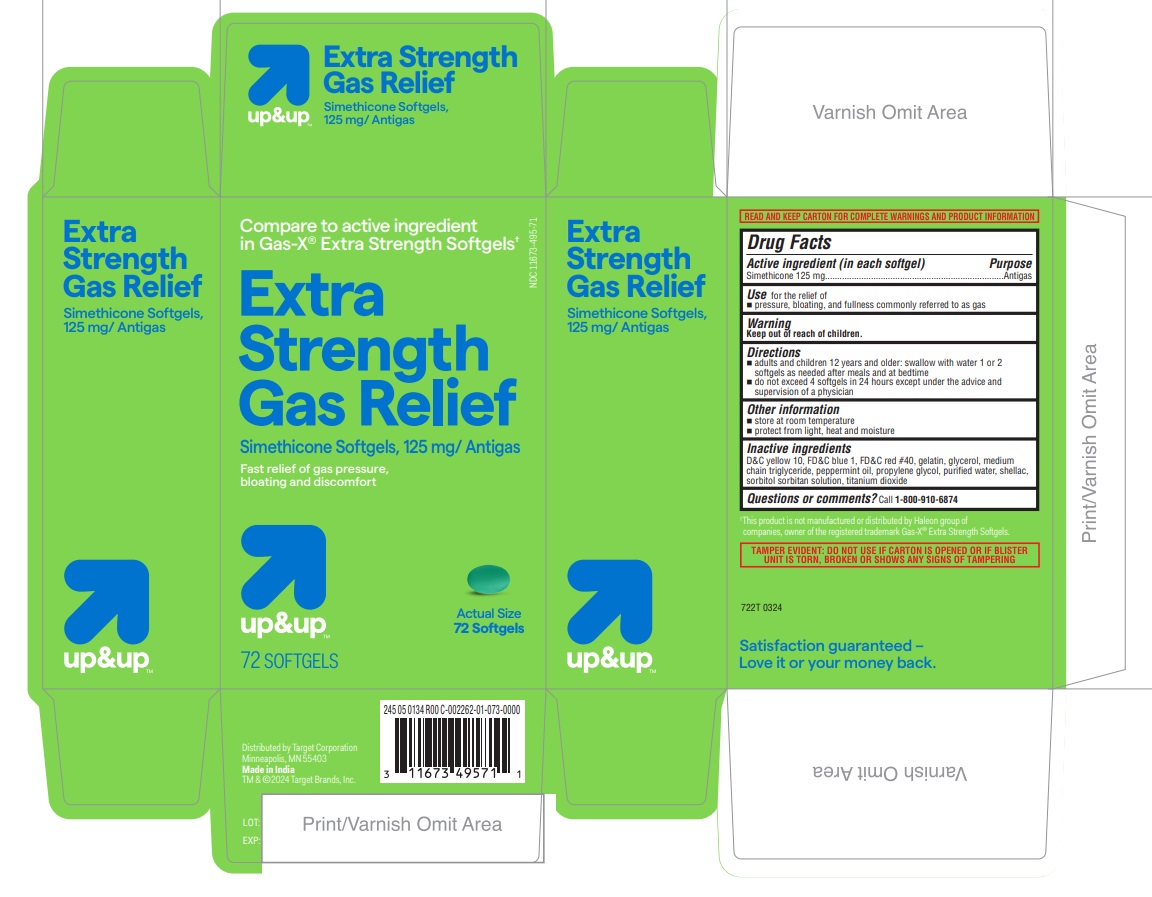 DRUG LABEL: Extra Strength Gas Relief
NDC: 11673-495 | Form: CAPSULE, LIQUID FILLED
Manufacturer: TARGET CORPORATION
Category: otc | Type: HUMAN OTC DRUG LABEL
Date: 20250131

ACTIVE INGREDIENTS: DIMETHICONE 125 mg/1 1
INACTIVE INGREDIENTS: MEDIUM-CHAIN TRIGLYCERIDES; FD&C RED NO. 40; PEPPERMINT OIL; SORBITOL; TITANIUM DIOXIDE; FD&C BLUE NO. 1; GELATIN; GLYCERIN; D&C YELLOW NO. 10; WATER; SHELLAC; SORBITAN; PROPYLENE GLYCOL

722T Target 11673-495 Simethicone 125 mg softgels

Active ingredient (in each softgel)

Simethicone 125 mg

Purpose

Anti-gas

INDICATIONS AND USAGE

Use for the relief of

- pressure, bloating and fullness commonly referred to as gas

Warning

Keep out of reach of children.

Directions

- adults and children 12 years and older: swallow with water 1 or 2 softgels as needed after meals and at bedtime
- do not exceed 4 softgels in 24 hours except under the advice and supervision of a physician

Other information

- store at room temperature
- protect from light, heat and moisture

Inactive ingredients

D&C Yellow #10, FD&C Blue 1, FD&C Red #40, gelatin, glycerol, medium chain triglyceride, peppermint oil, propylene glycol, purified water, shellac, sorbitol sorbitan solution, titanium dioxide

Questions or comments? Call 1-800-910-6874